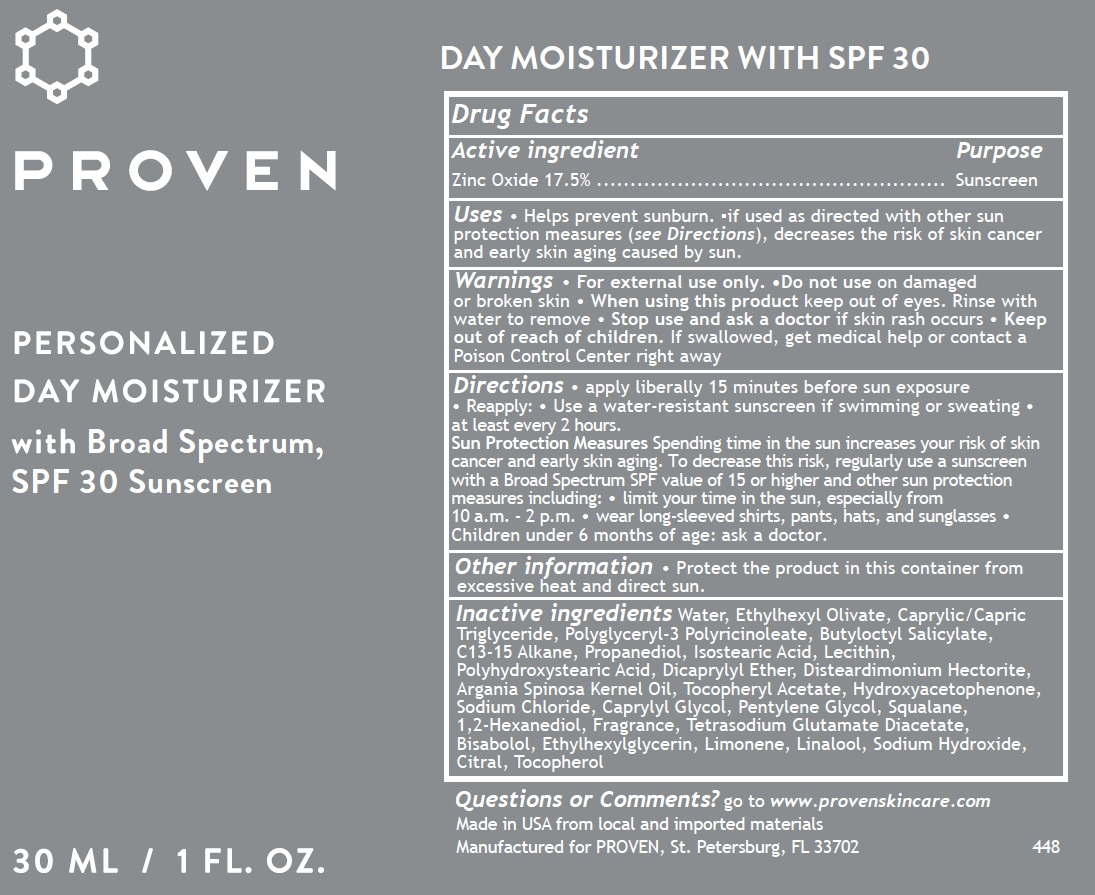 DRUG LABEL: Proven Personalized Day Moisturizer Sunscreen SPF 30
NDC: 73572-008 | Form: CREAM
Manufacturer: Proven Skincare
Category: otc | Type: HUMAN OTC DRUG LABEL
Date: 20250620

ACTIVE INGREDIENTS: ZINC OXIDE 175 mg/1 mL
INACTIVE INGREDIENTS: WATER; ETHYLHEXYL OLIVATE; MEDIUM-CHAIN TRIGLYCERIDES; BUTYLOCTYL SALICYLATE; C13-15 ALKANE; PROPANEDIOL; ISOSTEARIC ACID; DICAPRYLYL ETHER; DISTEARDIMONIUM HECTORITE; ARGANIA SPINOSA KERNEL OIL; .ALPHA.-TOCOPHEROL ACETATE; HYDROXYACETOPHENONE; SODIUM CHLORIDE; CAPRYLYL GLYCOL; PENTYLENE GLYCOL; SQUALANE; 1,2-HEXANEDIOL; TETRASODIUM GLUTAMATE DIACETATE; BISABOLOL; ETHYLHEXYLGLYCERIN; LIMONENE, (+)-; LINALOOL, (+/-)-; SODIUM HYDROXIDE; CITRAL; TOCOPHEROL

Proven Personalized Day Moisturizer Sunscreen SPF 30

Active ingredient

Zinc Oxide 17.5%

Purpose

Sunscreen

Uses

- Helps prevent sunburn.
- if used as directed with other sun protection measures (see Directions), decreases the risk of skin cancer and early skin aging caused by sun.

Warnings

- For external use only

Do not use

- on damaged or broken skin

When using this product

- keep out of eyes. Rinse with water to remove

Stop use and ask a doctor

if skin rash occurs

Keep out of reach of children.

If swallowed, get medical help or contact a Poison Control Center right away

Directions

- apply liberally 15 minutes before sun exposure
- Reapply: • Use a water-resistant sunscreen if swimming or sweating
- at least every 2 hours.
- Sun Protection MeasuresSpending time in the sun increases your risk of skin cancer and early skin aging. To decrease this risk, regularly use a sunscreen with a Broad Spectrum SPF value of 15 or higher and other sun protection measures including:
- limit your time in the sun, especially from10 a.m. - 2 p.m.
- wear long-sleeved shirts, pants, hats, and sunglasses
- Children under 6 months of age: ask a doctor.

Other information

- Protect the product in this container from excessive heat and direct sun.

Inactive ingredients

Water, Ethylhexyl Olivate, Caprylic/Capric Triglyceride, Polyglyceryl-3 Polyricinoleate, Butyloctyl Salicylate, C13-15 Alkane, Propanediol, Isostearic Acid, Lecithin, Polyhydroxystearic Acid, Dicaprylyl Ether, Disteardimonium Hectorite, Argania Spinosa Kernel Oil, Tocopheryl Acetate, Hydroxyacetophenone, Sodium Chloride, Caprylyl Glycol, Pentylene Glycol, Squalane, 1,2-Hexanediol, Fragrance, Tetrasodium Glutamate Diacetate, Bisabolol, Ethylhexylglycerin, Limonene, Linalool, Sodium Hydroxide, Citral, Tocopherol

Questions or Comments?

go to www.provenskincare.com